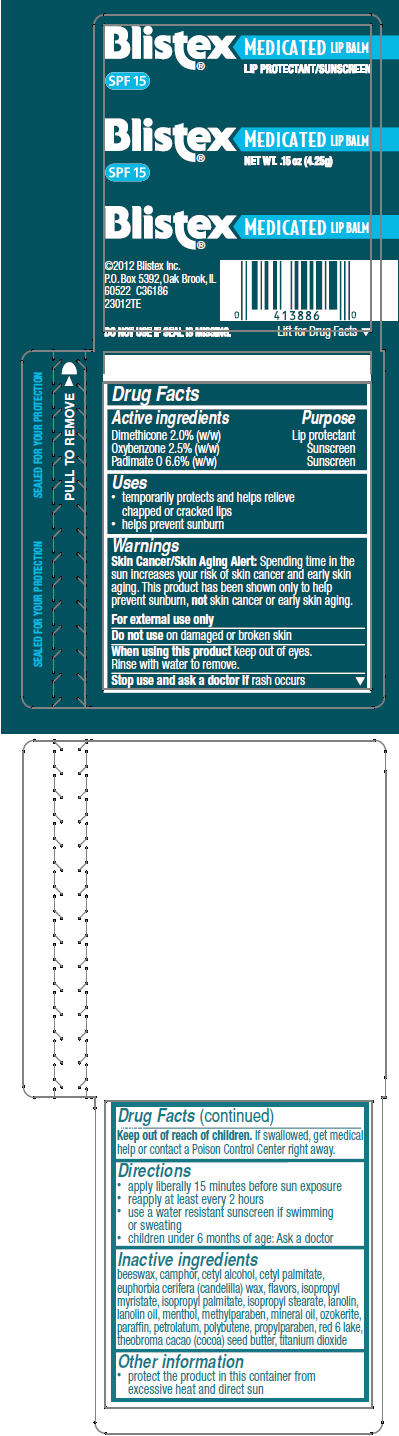 DRUG LABEL: Blistex 
NDC: 10157-9822 | Form: STICK
Manufacturer: Blistex Inc.
Category: otc | Type: HUMAN OTC DRUG LABEL
Date: 20181120

ACTIVE INGREDIENTS: Dimethicone 2 g/100 g; Oxybenzone 2.5 g/100 g; Padimate O 6.6 g/100 g
INACTIVE INGREDIENTS: yellow wax; cetyl alcohol; cetyl palmitate; candelilla wax; isopropyl myristate; isopropyl palmitate; isopropyl stearate; lanolin; lanolin oil; menthol, unspecified form; methylparaben; mineral oil; paraffin; petrolatum; polybutene (1400 MW); propylparaben; D&C Red No. 6; aluminum oxide; cocoa butter; titanium dioxide

Blistex®
Medicated Lip Balm

Drug Facts

ACTIVE INGREDIENT

Active ingredients | Purpose
Dimethicone 2.0% (w/w) | Lip protectant
Oxybenzone 2.5% (w/w) | Sunscreen
Padimate O 6.6% (w/w) | Sunscreen

Uses

- temporarily protects and helps relieve chapped or cracked lips
- helps prevent sunburn

Warnings

Skin Cancer/Skin Aging Alert

Spending time in the sun increases your risk of skin cancer and early skin aging. This product has been shown only to help prevent sunburn, not skin cancer or early skin aging.

For external use only

Do not use on damaged or broken skin

When using this product keep out of eyes.

Rinse with water to remove.

Stop use and ask a doctor if rash occurs

Keep out of reach of children. If swallowed, get medical help or contact a Poison Control Center right away.

Directions

- apply liberally 15 minutes before sun exposure
- reapply at least every 2 hours
- use a water resistant sunscreen if swimming or sweating
- children under 6 months of age: Ask a doctor

Inactive ingredients

beeswax, camphor, cetyl alcohol, cetyl palmitate, euphorbia cerifera (candelilla) wax, flavors, isopropyl myristate, isopropyl palmitate, isopropyl stearate, lanolin, lanolin oil, menthol, methylparaben, mineral oil, ozokerite, paraffin, petrolatum, polybutene, propylparaben, red 6 lake, theobroma cacao (cocoa) seed butter, titanium dioxide

Other information

- protect the product in this container from excessive heat and direct sun

PRINCIPAL DISPLAY PANEL - 4.25 g Cylinder Blister Pack

Blistex® MEDICATED LIP BALM
LIP PROTECTANT/SUNSCREEN

SPF 15

Blistex® MEDICATED LIP BALM
NET WT. .15 oz (4.25g)

SPF 15

Blistex® MEDICATED LIP BALM

©2012 Blistex Inc.
P.O. Box 5392, Oak Brook, IL
60522 C36186
23012TE

DO NOT USE IF SEAL IS MISSING.

Lift for Drug Facts